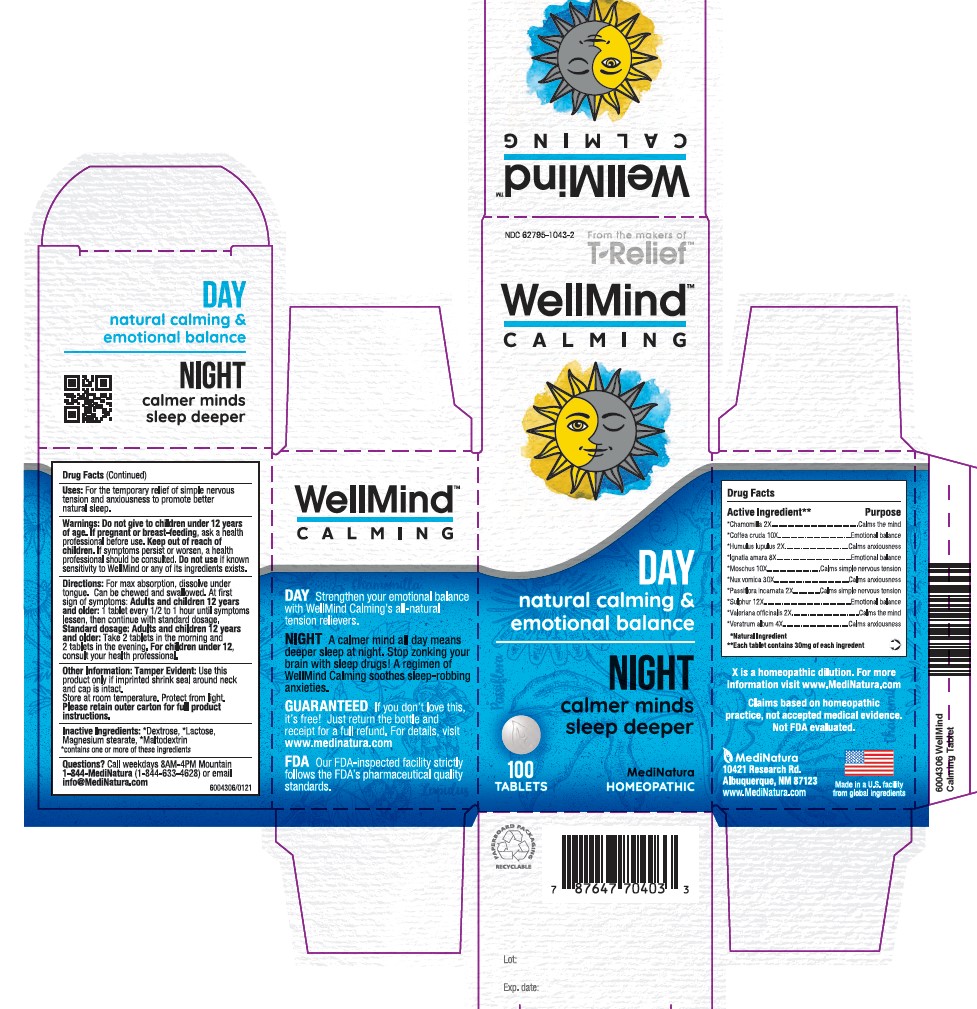 DRUG LABEL: WellMind Calming
NDC: 62795-1043 | Form: TABLET
Manufacturer: MediNatura Inc
Category: homeopathic | Type: HUMAN OTC DRUG LABEL
Date: 20230419

ACTIVE INGREDIENTS: MATRICARIA CHAMOMILLA WHOLE 2 [hp_X]/1 1; ARABICA COFFEE BEAN 10 [hp_X]/1 1; HOPS 2 [hp_X]/1 1; STRYCHNOS IGNATII SEED 8 [hp_X]/1 1; MOSCHUS MOSCHIFERUS MUSK SAC RESIN 10 [hp_X]/1 1; STRYCHNOS NUX-VOMICA SEED 30 [hp_X]/1 1; PASSIFLORA INCARNATA FLOWERING TOP 2 [hp_X]/1 1; SULFUR 12 [hp_X]/1 1; VALERIAN 2 [hp_X]/1 1; VERATRUM ALBUM ROOT 4 [hp_X]/1 1
INACTIVE INGREDIENTS: LACTOSE, UNSPECIFIED FORM; MAGNESIUM STEARATE; MALTODEXTRIN; DEXTROSE, UNSPECIFIED FORM

WellMind Calming

KEEP OUT OF REACH OF CHILDREN

Uses

For the temporary relief of simple nervous tension and anxiousness to promote better natural sleep.

WARNINGS

Warnings: Do not give to children under 12 years of age.If pregnant or breast-feeding, ask a health professional before use. KEEP OUTOF REACH OF CHILDREN. If symptoms persist or worsen, a health professional should be consulted. Do not use if known sensitivity to WellMind or any of it's ingredients exists.

DIRECTIONS

For max absorption, dissolve under tongue. Can be chewed and swallowed. At first sign of symptoms: Adults and children 12 years and older: 1 tablet every ½ to 1 hour until symptoms lessen, then continue with standard dosage.Standard dosage: Adults and children 12 years and older: take 2 tablets in the moning and 2 tablets in the evening. For children under 12 years, consult your health professional.

PURPOSE

Calmer Minds

Sleep Deeper

ACTIVE INGREDIENTS

Chamomilla 2X, Coffea cruda 10X, Humulus lupulus 2X, Ignatia amara 8X, Moschus 10X,
Nux-vomoica 30X, Passiflora incarnata 2X, Sulphur 12X, Valeriana officinalis 2X, Veratrum album 4X

INACTIVE INGREDIENTS

*Dextrose, *Lactose, Magnesium Stearate, *Maltodextrin
*contains one or more of these ingredients.

PACKAGE LABEL

Add image transcription here...